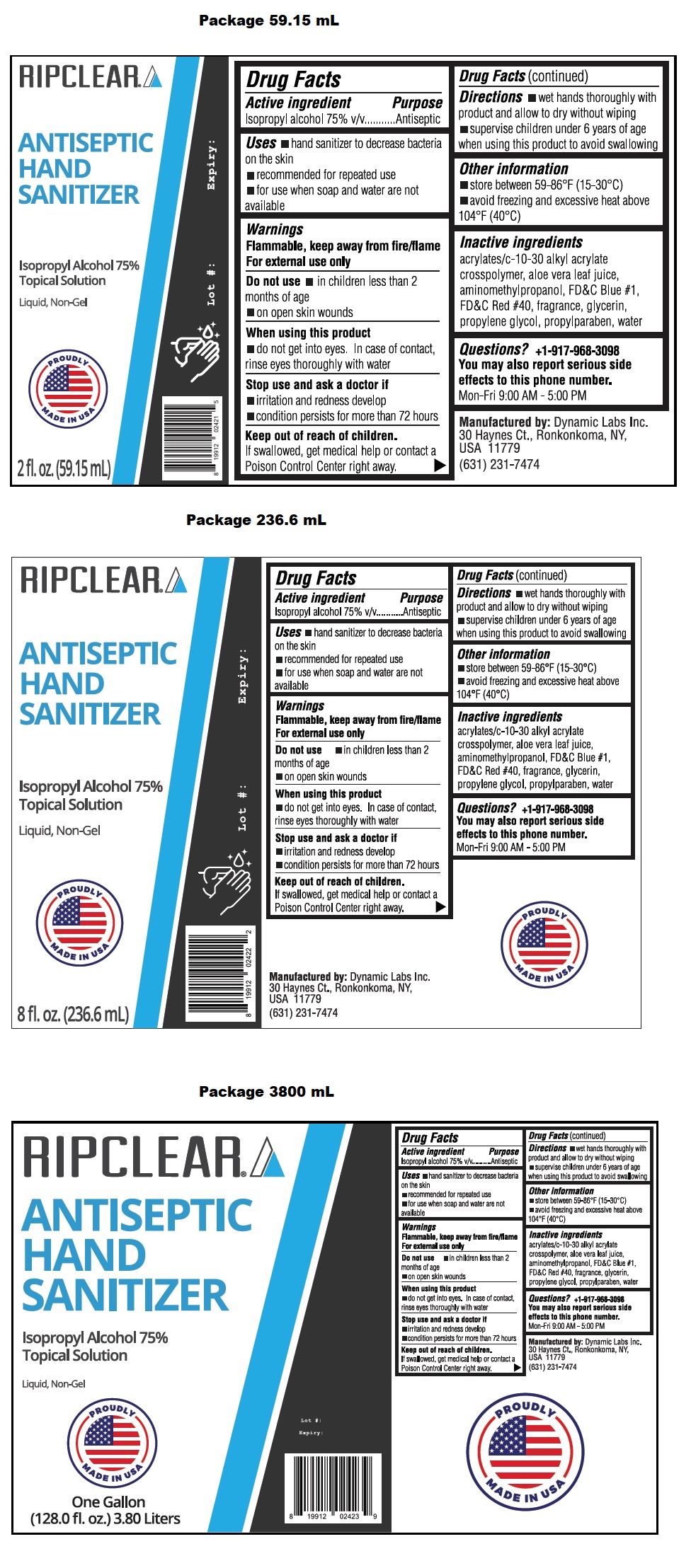 DRUG LABEL: RIPCLEAR ANTISEPTIC HAND SANITIZER
NDC: 80555-001 | Form: LIQUID
Manufacturer: Rip Clear LLC
Category: otc | Type: HUMAN OTC DRUG LABEL
Date: 20201005

ACTIVE INGREDIENTS: ISOPROPYL ALCOHOL 75 mL/100 mL
INACTIVE INGREDIENTS: CARBOMER INTERPOLYMER TYPE A (ALLYL SUCROSE CROSSLINKED); ALOE VERA LEAF; AMINOMETHYLPROPANOL; FD&C BLUE NO. 1; FD&C RED NO. 40; GLYCERIN; PROPYLENE GLYCOL; PROPYLPARABEN; WATER

RIPCLEAR® ANTISEPTIC HAND SANITIZER

Active ingredient

Isopropyl alcohol 75% v/v

Purpose

Antiseptic

INDICATIONS AND USAGE

Uses • hand sanitizer to decrease bacteria on the skin • recommended for repeated use • for use when soap and water are not available

Warnings

Flammable, keep away from fire/flame
For external use only

Do not use • in children less than 2 months of age • on open skin wounds

When using this product • do not get into eyes. In case of contact, rinse eyes thoroughly with water

Stop use and ask a doctor if • irritation and redness develop • condition persists for more than 72 hours

Keep out of reach of children. If swallowed get a medical help or contact a Poison Control Center right away.

DOSAGE AND ADMINISTRATION

Directions • wet hands thoroughly with product and allow to dry without wiping • supervise children under 6 years of age when using this product to avoid swallowing

Other information

• store between 59-86°F (15-30°C) • avoid freezing and excessive heat above 104°F (40°C)

Inactive ingredients

acrylates/c-10-30 alkyl acrylate crosspolymer, aloe vera leaf juice, aminomethylpropanol, FD&C Blue #1, FD&C Red #40, fragrance, glycerin, propylene glycol, propylparaben, water

Questions? +1-917-968-3098

You may also report serious side effects to this phone number.

Mon-Fri 9:00 AM - 5:00 PM

Topical solution

Liquid, Non-Gel

PROUDLY MADE IN USA

Manufactured by: Dynamic Labs Inc.
30 Haynes Ct., Ronkonkoma, NY, USA 11779
(631) 231-7474